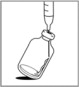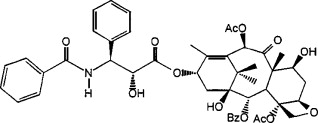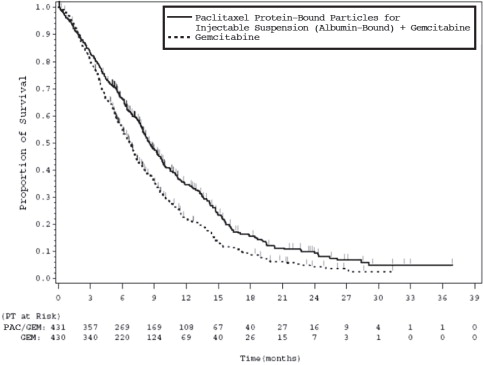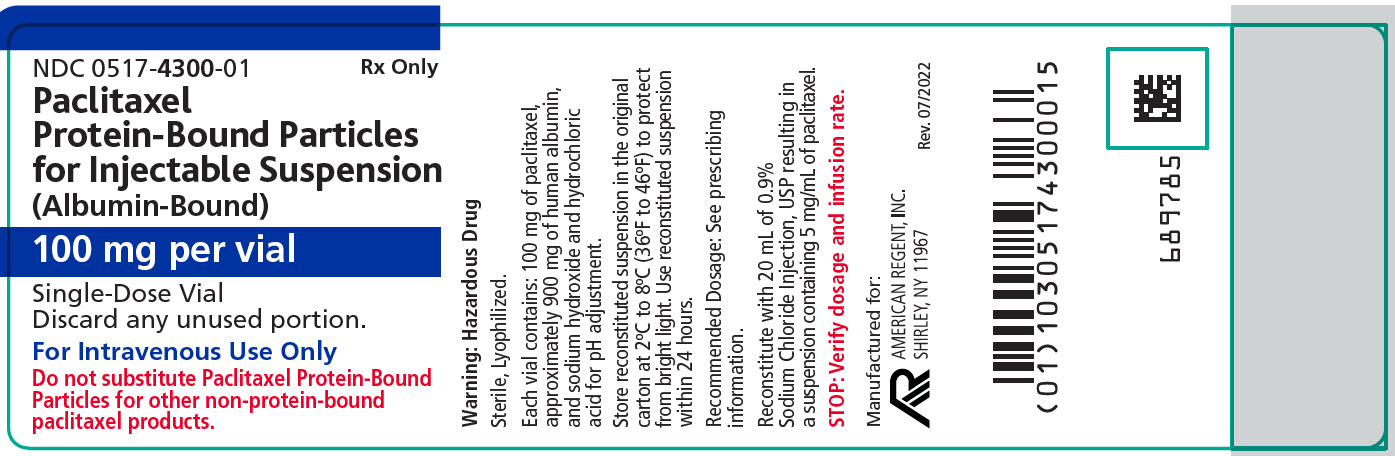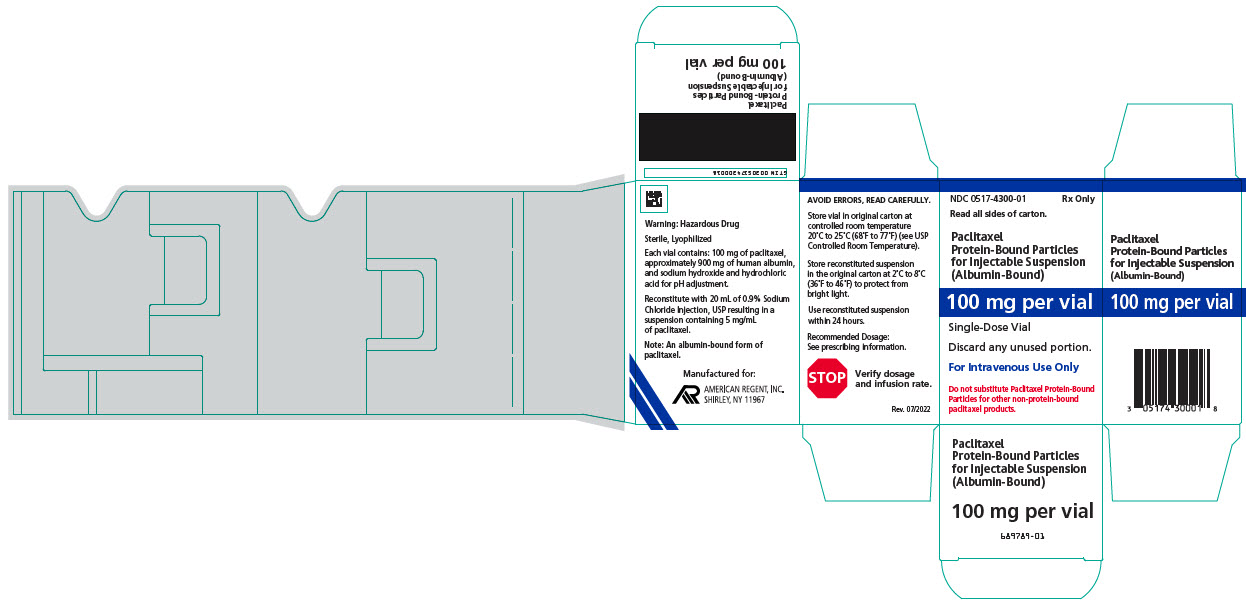 DRUG LABEL: PACLITAXEL PROTEIN BOUND PARTICLES ALBUMIN BOUND
NDC: 0517-4300 | Form: INJECTION, POWDER, LYOPHILIZED, FOR SUSPENSION
Manufacturer: American Regent, Inc.
Category: prescription | Type: HUMAN PRESCRIPTION DRUG LABEL
Date: 20230501

ACTIVE INGREDIENTS: PACLITAXEL 100 mg/20 mL
INACTIVE INGREDIENTS: ALBUMIN HUMAN; SODIUM HYDROXIDE; HYDROCHLORIC ACID

HIGHLIGHTS OF PRESCRIBING INFORMATION

These highlights do not include all the information needed to use PACLITAXEL PROTEIN-BOUND PARTICLES FOR INJECTABLE SUSPENSION (ALBUMIN-BOUND) safely and effectively. See full prescribing information for PACLITAXEL PROTEIN-BOUND PARTICLES FOR INJECTABLE SUSPENSION (ALBUMIN-BOUND).
PACLITAXEL PROTEIN-BOUND PARTICLES FOR INJECTABLE SUSPENSION (ALBUMIN-BOUND), for intravenous use
Initial U.S. Approval: 2005

WARNING: SEVERE MYELOSUPPRESSION

See full prescribing information for complete boxed warning.

- Do not administer Paclitaxel Protein-Bound Particles for Injectable Suspension (Albumin-Bound) therapy to patients with baseline neutrophil counts of less than 1,500 cells/mm^3. (4)
- Monitor for neutropenia, which may be severe and result in infection or sepsis. (5.1, 5.3)
- Perform frequent complete blood cell counts on all patients receiving Paclitaxel Protein-Bound Particles for Injectable Suspension (Albumin-Bound). (5.1, 5.3)

1 INDICATIONS AND USAGE

Paclitaxel Protein-Bound Particles for Injectable Suspension (Albumin-Bound) is a microtubule inhibitor indicated for the treatment of:

- Metastatic breast cancer, after failure of combination chemotherapy for metastatic disease or relapse within 6 months of adjuvant chemotherapy. Prior therapy should have included an anthracycline unless clinically contraindicated. (1.1)
- Locally advanced or metastatic non-small cell lung cancer (NSCLC), as first-line treatment in combination with carboplatin, in patients who are not candidates for curative surgery or radiation therapy. (1.2)
- Metastatic adenocarcinoma of the pancreas as first-line treatment, in combination with gemcitabine. (1.3)

2 DOSAGE AND ADMINISTRATION

- Do not substitute Paclitaxel Protein-Bound Particles for Injectable Suspension (Albumin-Bound) for other non-protein-bound paclitaxel products. (2.1)
- Extravasation: Closely monitor the infusion site for extravasation and infiltration. (2.1)
- Metastatic Breast Cancer (MBC): Recommended dosage of Paclitaxel Protein-Bound Particles for Injectable Suspension (Albumin-Bound) is 260 mg/m^2 intravenously over 30 minutes every 3 weeks. (2.2)
- Non-Small Cell Lung Cancer (NSCLC): Recommended dosage of Paclitaxel Protein-Bound Particles for Injectable Suspension (Albumin-Bound) is 100 mg/m^2 intravenously over 30 minutes on Days 1, 8, and 15 of each 21-day cycle; administer carboplatin on Day 1 of each 21-day cycle immediately after Paclitaxel Protein-Bound Particles for Injectable Suspension (Albumin-Bound). (2.2)
- Adenocarcinoma of the Pancreas: Recommended dosage of Paclitaxel Protein-Bound Particles for Injectable Suspension (Albumin-Bound) is 125 mg/m^2 intravenously over 30-40 minutes on Days 1, 8 and 15 of each 28-day cycle; administer gemcitabine on Days 1, 8 and 15 of each 28-day cycle immediately after Paclitaxel Protein-Bound Particles for Injectable Suspension (Albumin-Bound). (2.4)
- Use in Patients with Hepatic Impairment: Paclitaxel Protein-Bound Particles for Injectable Suspension (Albumin-Bound) is not recommended for use in patients with AST greater than 10 x the upper limit of normal (ULN); or bilirubin greater than 5 x ULN or patients with metastatic adenocarcinoma of the pancreas who have moderate to severe hepatic impairment. For MBC or NSCLC, reduce starting dose in patients with moderate to severe hepatic impairment. (2.5)
- Dose Reductions for Adverse Reactions: Dose reductions or discontinuation may be needed based on severe hematologic, neurologic, cutaneous, or gastrointestinal toxicities. (2.6)
- See Full Prescribing Information for instructions on reconstitution of lyophilized powder, and preparation and administration of the injection.

3 DOSAGE FORMS AND STRENGTHS

For injectable suspension: white to yellow, sterile, lyophilized powder containing 100 mg of paclitaxel formulated as albumin-bound particles in single-dose vial for reconstitution. (3)

4 CONTRAINDICATIONS

- Neutrophil counts of < 1,500 cells/mm^3. (4)
- Severe hypersensitivity reactions to Paclitaxel Protein-Bound Particles for Injectable Suspension (Albumin-Bound). (4)

5 WARNINGS AND PRECAUTIONS

- Sensory neuropathy occurs frequently and may require dose reduction or treatment interruption. (5.2)
- Sepsis occurred in patients with or without neutropenia who received protein bound paclitaxel in combination with gemcitabine; interrupt Paclitaxel Protein-Bound Particles for Injectable Suspension (Albumin-Bound) and gemcitabine until sepsis resolves, and if neutropenia, until neutrophils are at least 1500 cells/mm^3, then resume treatment at reduced dose levels. (5.3)
- Pneumonitis occurred with the use of protein bound paclitaxel in combination with gemcitabine; permanently discontinue treatment with Paclitaxel Protein-Bound Particles for Injectable Suspension (Albumin-Bound) and gemcitabine. (5.4)
- Severe hypersensitivity reactions with fatal outcome have been reported. Do not rechallenge with this drug. (4, 5.5)
- Exposure and toxicity of paclitaxel can be increased in patients with hepatic impairment, consider dose reduction and closely monitor patients with hepatic impairment. (2.5, 5.6)
- Paclitaxel Protein-Bound Particles for Injectable Suspension (Albumin-Bound) contains albumin derived from human blood, which has a theoretical risk of viral transmission. (5.7)
- Paclitaxel Protein-Bound Particles for Injectable Suspension (Albumin-Bound) can cause fetal harm. Advise patients of potential risk to a fetus and to use effective contraception. (5.8, 8.1, 8.3)

6 ADVERSE REACTIONS

- The most common adverse reactions (≥ 20%) in metastatic breast cancer are alopecia, neutropenia, sensory neuropathy, abnormal ECG, fatigue/asthenia, myalgia/arthralgia, AST elevation, alkaline phosphatase elevation, anemia, nausea, infections, and diarrhea. (6.1)
- The most common adverse reactions (≥ 20%) in NSCLC are anemia, neutropenia, thrombocytopenia, alopecia, peripheral neuropathy, nausea, and fatigue. (6.1)
- The most common (≥ 20%) adverse reactions of protein bound paclitaxel in adenocarcinoma of the pancreas are neutropenia, fatigue, peripheral neuropathy, nausea, alopecia, peripheral edema, diarrhea, pyrexia, vomiting, decreased appetite, rash, and dehydration. (6.1)

To report SUSPECTED ADVERSE REACTIONS, contact American Regent, Inc. at 1-888-532-7998 or FDA at 1-800-FDA-1088 or www.fda.gov/medwatch.

7 DRUG INTERACTIONS

Use caution when concomitantly administering Paclitaxel Protein-Bound Particles for Injectable Suspension (Albumin-Bound) with inhibitors or inducers of either CYP2C8 or CYP3A4. (7)

8 USE IN SPECIFIC POPULATIONS

- Lactation: Advise not to breastfeed. (8.2)

FULL PRESCRIBING INFORMATION

Paclitaxel Protein-Bound Particles for Injectable Suspension (Albumin-Bound)

WARNING: SEVERE MYELOSUPPRESSION

- Do not administer Paclitaxel Protein-Bound Particles for Injectable Suspension (Albumin-Bound) therapy to patients who have baseline neutrophil counts of less than 1,500 cells/mm^3 [see Contraindications (4)].
- Monitor for neutropenia, which may be severe and result in infection or sepsis [see Warnings and Precautions (5.1, 5.3)].
- Perform frequent complete blood cell counts on all patients receiving Paclitaxel Protein-Bound Particles for Injectable Suspension (Albumin-Bound) [see Contraindications (4), Warnings and Precautions (5.1, 5.3)].

1 INDICATIONS AND USAGE

1.1 Metastatic Breast Cancer

Paclitaxel Protein-Bound Particles for Injectable Suspension (Albumin-Bound) is indicated for the treatment of breast cancer after failure of combination chemotherapy for metastatic disease or relapse within 6 months of adjuvant chemotherapy. Prior therapy should have included an anthracycline unless clinically contraindicated.

1.2 Non-Small Cell Lung Cancer

Paclitaxel Protein-Bound Particles for Injectable Suspension (Albumin-Bound) is indicated for the first-line treatment of locally advanced or metastatic non-small cell lung cancer, in combination with carboplatin, in patients who are not candidates for curative surgery or radiation therapy.

1.3 Adenocarcinoma of the Pancreas

Paclitaxel Protein-Bound Particles for Injectable Suspension (Albumin-Bound) is indicated for the first-line treatment of patients with metastatic adenocarcinoma of the pancreas, in combination with gemcitabine.

2 DOSAGE AND ADMINISTRATION

2.1 Important Administration Instructions

DO NOT SUBSTITUTE FOR OR WITH OTHER PACLITAXEL FORMULATIONS. Paclitaxel Protein-Bound Particles for Injectable Suspension (Albumin-Bound) has different dosage and administration instructions from other paclitaxel products.

Closely monitor the infusion site for extravasation or drug infiltration during administration. Limiting the infusion of Paclitaxel Protein-Bound Particles for Injectable Suspension (Albumin-Bound) to 30 minutes may reduce the risk of infusion-related reactions [see Adverse Reactions (6.2)].

Consider premedication in patients who have had prior hypersensitivity reactions to Paclitaxel Protein-Bound Particles for Injectable Suspension (Albumin-Bound). Do not re-challenge patients who experience a severe hypersensitivity reaction to Paclitaxel Protein-Bound Particles for Injectable Suspension (Albumin-Bound) [see Contraindications (4) and Warnings and Precautions (5.5)].

2.2 Recommended Dosage for Metastatic Breast Cancer

After failure of combination chemotherapy for metastatic breast cancer or relapse within 6 months of adjuvant chemotherapy, the recommended regimen for Paclitaxel Protein-Bound Particles for Injectable Suspension (Albumin-Bound) is 260 mg/m^2 administered intravenously over 30 minutes every 3 weeks.

2.3 Recommended Dosage for Non-Small Cell Lung Cancer

The recommended dose of Paclitaxel Protein-Bound Particles for Injectable Suspension (Albumin-Bound) is 100 mg/m^2 administered as an intravenous infusion over 30 minutes on Days 1, 8, and 15 of each 21-day cycle. Administer carboplatin on Day 1 of each 21-day cycle immediately after Paclitaxel Protein-Bound Particles for Injectable Suspension (Albumin-Bound) [see Clinical Studies (14.2)].

2.4 Recommended Dosage for Adenocarcinoma of the Pancreas

The recommended dose of Paclitaxel Protein-Bound Particles for Injectable Suspension (Albumin-Bound) is 125 mg/m^2 administered as an intravenous infusion over 30-40 minutes on Days 1, 8 and 15 of each 28-day cycle. Administer gemcitabine immediately after Paclitaxel Protein-Bound Particles for Injectable Suspension (Albumin-Bound) on Days 1, 8 and 15 of each 28-day cycle [see Clinical Studies (14.3)].

2.5 Dosage Modifications for Hepatic Impairment

For patients with moderate or severe hepatic impairment, reduce the starting dose of Paclitaxel Protein-Bound Particles for Injectable Suspension (Albumin-Bound) as shown in Table 1.

Table 1: Recommendations for Starting Dose in Patients with Moderate and Severe Hepatic Impairment
 | AST Levels |  | Bilirubin Levels | Paclitaxel Protein-Bound Particles for Injectable Suspension (Albumin-Bound) Dosea
 | AST Levels |  | Bilirubin Levels | MBC | NSCLC c | Adenocarcinoma of Pancreasc
Moderate | < 10 x ULN | AND | > 1.5 to ≤ 3 x ULN | 200 mg/m2 b | 80 mg/m2 b | not recommended
Severe | < 10 x ULN | AND | > 3 to ≤ 5 x ULN | 200 mg/m2 b | 80 mg/m2 b | not recommended
 | > 10 x ULN | OR | > 5 x ULN | not recommended | not recommended | not recommended
AST = Aspartate Aminotransferase; MBC = Metastatic Breast Cancer; NSCLC = Non-Small Cell Lung Cancer; ULN = Upper limit of normal.
a Dosage recommendations are for the first course of therapy. The need for further dose adjustments in subsequent courses should be based on individual tolerance.
b A dose increase to 260 mg/m^2 for patients with metastatic breast cancer or 100 mg/m^2 for patients with non-small cell lung cancer in subsequent courses should be considered if the patient tolerates the reduced dose for two cycles.
c Patients with bilirubin levels above the upper limit of normal were excluded from clinical trials for pancreatic or lung cancer.

2.6 Dosage Modifications for Adverse Reactions

Metastatic Breast Cancer

Patients who experience severe neutropenia (neutrophils less than 500 cells/mm^3 for a week or longer) or severe sensory neuropathy during Paclitaxel Protein-Bound Particles for Injectable Suspension (Albumin-Bound) therapy should have dosage reduced to 220 mg/m^2 for subsequent courses of Paclitaxel Protein-Bound Particles for Injectable Suspension (Albumin-Bound). For recurrence of severe neutropenia or severe sensory neuropathy, additional dose reduction should be made to 180 mg/m^2. For Grade 3 sensory neuropathy hold treatment until resolution to Grade 1 or 2, followed by a dose reduction for all subsequent courses of Paclitaxel Protein-Bound Particles for Injectable Suspension (Albumin-Bound) [see Contraindications (4), Warnings and Precautions (5.1, 5.2) and Adverse Reactions (6.1)].

Non-Small Cell Lung Cancer

- Do not administer Paclitaxel Protein-Bound Particles for Injectable Suspension (Albumin-Bound) on Day 1 of a cycle until absolute neutrophil count (ANC) is at least 1500 cells/mm^3 and platelet count is at least 100,000 cells/mm^3 [see Contraindications (4), Warnings and Precautions (5.1) and Adverse Reactions (6.1)].
- In patients who develop severe neutropenia or thrombocytopenia withhold treatment until counts recover to an absolute neutrophil count of at least 1500 cells/mm^3 and platelet count of at least 100,000 cells/mm^3 on Day 1 or to an absolute neutrophil count of at least 500 cells/mm^3 and platelet count of at least 50,000 cells/mm^3 on Days 8 or 15 of the cycle. Upon resumption of dosing, permanently reduce Paclitaxel Protein-Bound Particles for Injectable Suspension (Albumin-Bound) and carboplatin doses as outlined in Table 2.
- Withhold Paclitaxel Protein-Bound Particles for Injectable Suspension (Albumin-Bound) for Grade 3-4 peripheral neuropathy. Resume Paclitaxel Protein-Bound Particles for Injectable Suspension (Albumin-Bound) and carboplatin at reduced doses (see Table 2) when peripheral neuropathy improves to Grade 1 or completely resolves [see Warnings and Precautions (5.2) and Adverse Reactions (6.1)].

Table 2: Permanent Dose Reductions for Hematologic and Neurologic Adverse Reactions in NSCLC
Adverse Reaction | Occurrence | Weekly Paclitaxel Protein-Bound Particles for Injectable Suspension (Albumin-Bound) Dose (mg/m^2) | Every 3-Week Carboplatin Dose (AUC mg•min/mL)
Neutropenic Fever (ANC less than 500/mm^3 with fever >38°C) OR Delay of next cycle by more than 7 days for ANC less than 1500/mm^3 OR ANC less than 500/mm^3 for more than 7 days | First | 75 | 4.5
Neutropenic Fever (ANC less than 500/mm^3 with fever >38°C) OR Delay of next cycle by more than 7 days for ANC less than 1500/mm^3 OR ANC less than 500/mm^3 for more than 7 days | Second | 50 | 3
Neutropenic Fever (ANC less than 500/mm^3 with fever >38°C) OR Delay of next cycle by more than 7 days for ANC less than 1500/mm^3 OR ANC less than 500/mm^3 for more than 7 days | Third | Discontinue Treatment
Platelet count less than 50,000/mm^3 | First | 75 | 4.5
Platelet count less than 50,000/mm^3 | Second | Discontinue Treatment
Severe sensory Neuropathy – Grade 3 or 4 | First | 75 | 4.5
Severe sensory Neuropathy – Grade 3 or 4 | Second | 50 | 3
Severe sensory Neuropathy – Grade 3 or 4 | Third | Discontinue Treatment

Adenocarcinoma of the Pancreas

Dose level reductions for patients with adenocarcinoma of the pancreas, as referenced in Tables 4 and 5, are provided in Table 3.

Table 3: Dose Level Reductions for Patients with Adenocarcinoma of the Pancreas
Dose Level | Paclitaxel Protein-Bound Particles for Injectable Suspension (Albumin-Bound) (mg/m^2) | Gemcitabine (mg/m^2)
Full dose | 125 | 1,000
1st dose reduction | 100 | 800
2nd dose reduction | 75 | 600
If additional dose reduction required | Discontinue | Discontinue

Recommended dose modifications for neutropenia and thrombocytopenia for patients with adenocarcinoma of the pancreas are provided in Table 4.

Table 4: Dose Recommendation and Modifications for Neutropenia and/or Thrombocytopenia at the Start of a Cycle or within a Cycle for Patients with Adenocarcinoma of the Pancreas
Cycle Day | ANC (cells/mm^3) |  | Platelet count (cells/mm^3) | Paclitaxel Protein-Bound Particles for Injectable Suspension (Albumin-Bound) / Gemcitabine
Day 1 | < 1,500 | OR | < 100,000 | Delay doses until recovery
Day 8 | 500 to < 1,000 | OR | 50,000 to < 75,000 | Reduce 1 dose level
 | < 500 | OR | < 50,000 | Withhold doses
Day 15: If Day 8 doses were reduced or given without modification:
 | 500 to < 1,000 | OR | 50,000 to < 75,000 | Reduce 1 dose level from Day 8
 | < 500 | OR | < 50,000 | Withhold doses
Day 15: If Day 8 doses were withheld:
 | ≥ 1,000 | OR | ≥ 75,000 | Reduce 1 dose level from Day 1
 | 500 to < 1,000 | OR | 50,000 to < 75,000 | Reduce 2 dose levels from Day 1
 | < 500 | OR | < 50,000 | Withhold doses
ANC = Absolute Neutrophil Count

Recommended dose modifications for other adverse reactions in patients with adenocarcinoma of the pancreas are provided in Table 5.

Table 5: Dose Modifications for Other Adverse Reactions in Patients with Adenocarcinoma of the Pancreas
Adverse Reaction | Paclitaxel Protein-Bound Particles for Injectable Suspension (Albumin-Bound) | Gemcitabine
Febrile Neutropenia: Grade 3 or 4 | Withhold until fever resolves and ANC ≥ 1,500; resume at next lower dose level
Peripheral Neuropathy: Grade 3 or 4 | Withhold until improves to ≤ Grade 1; resume at next lower dose level | No dose reduction
Cutaneous Toxicity: Grade 2 or 3 | Reduce to next lower dose level; discontinue treatment if toxicity persists
Gastrointestinal Toxicity: Grade 3 mucositis or diarrhea | Withhold until improves to ≤ Grade 1; resume at next lower dose level

2.7 Preparation for Intravenous Administration

Paclitaxel Protein-Bound Particles for Injectable Suspension (Albumin-Bound) is a hazardous drug. Follow applicable special handling and disposal procedures.^1 The use of gloves is recommended. If Paclitaxel Protein-Bound Particles for Injectable Suspension (Albumin-Bound) (lyophilized cake or reconstituted suspension) contacts the skin, wash the skin immediately and thoroughly with soap and water. Following topical exposure to paclitaxel, events may include tingling, burning and redness. If Paclitaxel Protein-Bound Particles for Injectable Suspension (Albumin-Bound) contacts mucous membranes, the membranes should be flushed thoroughly with water.

Paclitaxel Protein-Bound Particles for Injectable Suspension (Albumin-Bound) is supplied as a sterile lyophilized powder for reconstitution before use.

Read the entire preparation instructions prior to reconstitution.

1. Aseptically, reconstitute each vial by injecting 20 mL of 0.9% Sodium Chloride Injection, USP.
2. Slowly inject the 20 mL of 0.9% Sodium Chloride Injection, USP, over a minimum of 1 minute, using the sterile syringe to direct the solution flow onto the INSIDE WALL OF THE VIAL.
3. DO NOT INJECT the 0.9% Sodium Chloride Injection, USP, directly onto the lyophilized cake as this will result in foaming.
4. Once the injection is complete, allow the vial to sit for a minimum of 5 minutes to ensure proper wetting of the lyophilized cake/powder.
5. Gently swirl and/or invert the vial slowly for at least 2 minutes until complete dissolution of any cake/powder occurs. Avoid generation of foam.
6. If foaming or clumping occurs, stand solution for at least 15 minutes until foam subsides.

Each mL of the reconstituted formulation will contain 5 mg/mL paclitaxel.

The reconstituted suspension should be milky and homogenous without visible particulates. If particulates or settling are visible, the vial should be gently inverted again to ensure complete resuspension prior to use. Discard the reconstituted suspension if precipitates are observed. Discard any unused portion.

Calculate the exact total dosing volume of 5 mg/mL suspension required for the patient and slowly withdraw the dosing volume of the reconstituted suspension from the vial(s) into a syringe: Dosing volume (mL)=Total dose (mg)/5 (mg/mL).

Inject the appropriate amount of reconstituted Paclitaxel Protein-Bound Particles for Injectable Suspension (Albumin-Bound) into an empty, sterile intravenous bag [plasticized polyvinyl chloride (PVC) containers, PVC or non-PVC type intravenous bag]. The use of specialized DEHP-free solution containers or administration sets is not necessary to prepare or administer Paclitaxel Protein-Bound Particles for Injectable Suspension (Albumin-Bound) infusions. The use of medical devices containing silicone oil as a lubricant (i.e., syringes and intravenous bags) to reconstitute and administer Paclitaxel Protein-Bound Particles for Injectable Suspension (Albumin-Bound) may result in the formation of proteinaceous strands.

Visually inspect the reconstituted Paclitaxel Protein-Bound Particles for Injectable Suspension (Albumin-Bound) suspension in the intravenous bag prior to administration. Discard the reconstituted suspension if proteinaceous strands, particulate matter or discoloration are observed.

2.8 Stability

Unopened vials of Paclitaxel Protein-Bound Particles for Injectable Suspension (Albumin-Bound) are stable until the date indicated on the package when stored between 20ºC to 25ºC (68ºF to 77ºF) (see USP Controlled Room Temperature) in the original package. Neither freezing nor refrigeration adversely affects the stability of the product.

Stability of Reconstituted Suspension in the Vial

Reconstituted Paclitaxel Protein-Bound Particles for Injectable Suspension (Albumin-Bound) in the vial should be used immediately, but may be refrigerated at 2ºC to 8ºC (36ºF to 46ºF) for a maximum of 24 hours if necessary. If not used immediately, each vial of reconstituted suspension should be replaced in the original carton to protect it from bright light. Discard any unused portion.

Stability of Reconstituted Suspension in the Infusion Bag

The suspension for infusion when prepared as recommended in an infusion bag should be used immediately, but may be refrigerated at 2°C to 8°C (36°F to 46°F) and protected from bright light for a maximum of 24 hours.

The total combined refrigerated storage time of reconstituted Paclitaxel Protein-Bound Particles for Injectable Suspension (Albumin-Bound) in the vial and in the infusion bag is 24 hours. This may be followed by storage in the infusion bag at ambient temperature (approximately 25°C) and lighting conditions for a maximum of 4 hours.

Discard any unused portion.

3 DOSAGE FORMS AND STRENGTHS

For injectable suspension, for intravenous use: white to yellow, sterile lyophilized powder containing 100 mg of paclitaxel formulated as albumin-bound particles in single-dose vial for reconstitution.

4 CONTRAINDICATIONS

Paclitaxel Protein-Bound Particles for Injectable Suspension (Albumin-Bound) is contraindicated in patients with:

- Baseline neutrophil counts of < 1,500 cells/mm^3 [see Warnings and Precautions (5.1)]
- A history of severe hypersensitivity reactions to Paclitaxel Protein-Bound Particles for Injectable Suspension (Albumin-Bound) [see Warnings and Precautions (5.5)]

5 WARNINGS AND PRECAUTIONS

5.1 Severe Myelosuppression

Severe myelosuppression (primarily neutropenia) is dose-dependent and a dose-limiting toxicity of protein bound paclitaxel. In clinical studies, Grade 3-4 neutropenia occurred in 34% of patients with metastatic breast cancer (MBC), 47% of patients with non-small cell lung cancer (NSCLC), and 38% of patients with pancreatic cancer.

Monitor for severe neutropenia and thrombocytopenia by performing complete blood cell counts frequently, including prior to dosing on Day 1 (for MBC) and Days 1, 8, and 15 (for NSCLC and for pancreatic cancer). Do not administer Paclitaxel Protein-Bound Particles for Injectable Suspension (Albumin-Bound) to patients with baseline absolute neutrophil counts (ANC) of less than 1,500 cells/mm^3 [see Contraindications (4)].

In the case of severe neutropenia (<500 cells/mm^3 for seven days or more) during a course of Paclitaxel Protein-Bound Particles for Injectable Suspension (Albumin-Bound) therapy, reduce the dose of Paclitaxel Protein-Bound Particles for Injectable Suspension (Albumin-Bound) in subsequent courses in patients with either MBC or NSCLC.

In patients with MBC, resume treatment with every-3-week cycles of Paclitaxel Protein-Bound Particles for Injectable Suspension (Albumin-Bound) after ANC recovers to a level >1,500 cells/mm^3 and platelets recover to a level >100,000 cells/mm^3. In patients with NSCLC, resume treatment if recommended at permanently reduced doses for both weekly Paclitaxel Protein-Bound Particles for Injectable Suspension (Albumin-Bound) and every-3-week carboplatin after ANC recovers to at least 1500 cells/mm^3 and platelet count of at least 100,000 cells/mm^3 on Day 1 or to an ANC of at least 500 cells/mm^3 and platelet count of at least 50,000 cells/mm^3 on Days 8 or 15 of the cycle [see Dosage and Administration (2.6)].

In patients with adenocarcinoma of the pancreas, withhold Paclitaxel Protein-Bound Particles for Injectable Suspension (Albumin-Bound) and gemcitabine if the ANC is less than 500 cells/mm^3 or platelets are less than 50,000 cells/mm^3 and delay initiation of the next cycle if the ANC is less than 1500 cells/mm^3 or platelet count is less than 100,000 cells/mm^3 on Day 1 of the cycle. Resume treatment with appropriate dose reduction if recommended [see Dosage and Administration (2.6)].

5.2 Severe Neuropathy

Sensory neuropathy is dose- and schedule-dependent [see Adverse Reactions (6.1)]. If ≥ Grade 3 sensory neuropathy develops, withhold Paclitaxel Protein-Bound Particles for Injectable Suspension (Albumin-Bound) treatment until resolution to Grade 1 or 2 for metastatic breast cancer or until resolution to ≤ Grade 1 for NSCLC and pancreatic cancer followed by a dose reduction for all subsequent courses of Paclitaxel Protein-Bound Particles for Injectable Suspension (Albumin-Bound) [see Dosage and Administration (2.6)].

5.3 Sepsis

Sepsis occurred in 5% of patients with or without neutropenia who received protein bound paclitaxel in combination with gemcitabine. Biliary obstruction or presence of biliary stent were risk factors for severe or fatal sepsis.

If a patient becomes febrile (regardless of ANC) initiate treatment with broad spectrum antibiotics. For febrile neutropenia, interrupt Paclitaxel Protein-Bound Particles for Injectable Suspension (Albumin-Bound) and gemcitabine until fever resolves and ANC ≥ 1500, then resume treatment at reduced dose levels [see Dosage and Administration (2.6)].

5.4 Pneumonitis

Pneumonitis, including some cases that were fatal, occurred in 4% of patients receiving protein bound paclitaxel in combination with gemcitabine.

Monitor patients for signs and symptoms of pneumonitis and interrupt Paclitaxel Protein-Bound Particles for Injectable Suspension (Albumin-Bound) and gemcitabine during evaluation of suspected pneumonitis. After ruling out infectious etiology and upon making a diagnosis of pneumonitis, permanently discontinue treatment with Paclitaxel Protein-Bound Particles for Injectable Suspension (Albumin-Bound) and gemcitabine.

5.5 Severe Hypersensitivity

Severe and sometimes fatal hypersensitivity reactions, including anaphylactic reactions, have been reported. Do not rechallenge patients who experience a severe hypersensitivity reaction to Paclitaxel Protein-Bound Particles for Injectable Suspension (Albumin-Bound) with this drug [see Contraindications (4)].

Cross-hypersensitivity between protein bound paclitaxel and other taxane products has been reported and may include severe reactions such as anaphylaxis. Closely monitor patients with a previous history of hypersensitivity to other taxanes during initiation of Paclitaxel Protein-Bound Particles for Injectable Suspension (Albumin-Bound) therapy.

5.6 Use in Patients with Hepatic Impairment

The exposure and toxicity of paclitaxel can be increased in patients with hepatic impairment. Closely monitor patients with hepatic impairment for severe myelosuppression

Paclitaxel Protein-Bound Particles for Injectable Suspension (Albumin-Bound) is not recommended in patients who have total bilirubin >5 x ULN or AST >10 x ULN. In addition, Paclitaxel Protein-Bound Particles for Injectable Suspension (Albumin-Bound) is not recommended in patients with metastatic adenocarcinoma of the pancreas who have moderate to severe hepatic impairment (total bilirubin >1.5 x ULN and AST ≤10 x ULN). Reduce the starting dose for patients with moderate or severe hepatic impairment [see Dosage and Administration (2.5), Use in Specific Populations (8.7), Clinical Pharmacology (12.3)].

5.7 Albumin (Human)

Paclitaxel Protein-Bound Particles for Injectable Suspension (Albumin-Bound) contains albumin (human), a derivative of human blood. Based on effective donor screening and product manufacturing processes, it carries a remote risk for transmission of viral diseases. A theoretical risk for transmission of Creutzfeldt-Jakob Disease (CJD) also is considered extremely remote. No cases of transmission of viral diseases or CJD have ever been identified for albumin.

5.8 Embryo-Fetal Toxicity

Based on mechanism of action and findings in animals, Paclitaxel Protein-Bound Particles for Injectable Suspension (Albumin-Bound) can cause fetal harm when administered to a pregnant woman. In animal reproduction studies, administration of protein bound paclitaxel to rats during pregnancy at doses lower than the maximum recommended human dose, based on body surface area, caused embryo-fetal toxicities, including intrauterine mortality, increased resorptions, reduced numbers of live fetuses, and malformations.

Advise females of reproductive potential of the potential risk to a fetus. Advise females of reproductive potential to use effective contraception and avoid becoming pregnant during treatment with Paclitaxel Protein-Bound Particles for Injectable Suspension (Albumin-Bound) and for at least six months after the last dose [see Use in Specific Populations (8.1, 8.3), Clinical Pharmacology (12.1)].

Based on findings from genetic toxicity and animal reproduction studies, advise male patients with female partners of reproductive potential to use effective contraception and avoid fathering a child during treatment with Paclitaxel Protein-Bound Particles for Injectable Suspension (Albumin-Bound) and for at least three months after the last dose [see Use in Specific Populations (8.1, 8.3), Nonclinical Toxicology (13.1)].

6 ADVERSE REACTIONS

Because clinical trials are conducted under widely varying conditions, adverse reaction rates observed in the clinical trials of a drug cannot be directly compared to rates in the clinical trials of another drug and may not reflect the rates observed in practice.

The most common adverse reactions (≥ 20%) with single-agent use of protein bound paclitaxel in metastatic breast cancer are alopecia, neutropenia, sensory neuropathy, abnormal ECG, fatigue/asthenia, myalgia/arthralgia, AST elevation, alkaline phosphatase elevation, anemia, nausea, infections, and diarrhea [see Adverse Reactions (6.1)].

The most common adverse reactions (≥ 20%) of protein bound paclitaxel in combination with carboplatin for non-small cell lung cancer are anemia, neutropenia, thrombocytopenia, alopecia, peripheral neuropathy, nausea, and fatigue [see Adverse Reactions (6.1)]. The most common serious adverse reactions of protein bound paclitaxel in combination with carboplatin for non-small cell lung cancer are anemia (4%) and pneumonia (3%). The most common adverse reactions resulting in permanent discontinuation of protein bound paclitaxel are neutropenia (3%), thrombocytopenia (3%), and peripheral neuropathy (1%). The most common adverse reactions resulting in dose reduction of protein bound paclitaxel are neutropenia (24%), thrombocytopenia (13%), and anemia (6%). The most common adverse reactions leading to withholding or delay in protein bound paclitaxel dosing are neutropenia (41%), thrombocytopenia (30%), and anemia (16%).

In a randomized open-label trial of protein bound paclitaxel in combination with gemcitabine for pancreatic adenocarcinoma [see Clinical Studies (14.3)], the most common (≥ 20%) selected (with a ≥ 5% higher incidence) adverse reactions of protein bound paclitaxel are neutropenia, fatigue, peripheral neuropathy, nausea, alopecia, peripheral edema, diarrhea, pyrexia, vomiting, decreased appetite, rash, and dehydration [see Adverse Reactions (6.1)]. The most common serious adverse reactions of protein bound paclitaxel (with a ≥ 1% higher incidence) are pyrexia (6%), dehydration (5%), pneumonia (4%), and vomiting (4%). The most common adverse reactions resulting in permanent discontinuation of protein bound paclitaxel are peripheral neuropathy (8%), fatigue (4%), and thrombocytopenia (2%). The most common adverse reactions resulting in dose reduction of protein bound paclitaxel are neutropenia (10%) and peripheral neuropathy (6%). The most common adverse reactions leading to withholding or delay in protein bound paclitaxel dosing are neutropenia (16%), thrombocytopenia (12%), fatigue (8%), peripheral neuropathy (15%), anemia (5%), and diarrhea (5%).

6.1 Clinical Trials Experience

Metastatic Breast Cancer

Table 6 shows the frequency of important adverse reactions in the randomized comparative trial for the patients who received either single-agent protein bound paclitaxel or paclitaxel injection for the treatment of metastatic breast cancer.

Table 6: Adverse Reactions in the Randomized Metastatic Breast Cancer Study on an Every-3-Weeks Schedule
 | Percent of Patients
 | Protein-Bound Paclitaxel 260 mg/m^2 over 30 min (n=229) | Paclitaxel Injection 175 mg/m^2 over 3 ha (n=225)
Bone Marrow
Neutropenia < 2.0 x 10^9/L < 0.5 x 10^9/L
Neutropenia < 2.0 x 10^9/L < 0.5 x 10^9/L | 80 9 | 82 22
Thrombocytopenia < 100 x 10^9/L < 50 x 10^9/L
Thrombocytopenia < 100 x 10^9/L < 50 x 10^9/L | 2 <1 | 3 <1
Anemia
< 11 g/dL | 33 | 25
< 8 g/dL | 1 | <1
Infections | 24 | 20
Febrile Neutropenia | 2 | 1
Neutropenic Sepsis | <1 | <1
Bleeding | 2 | 2
Hypersensitivity Reactionb
All | 4 | 12
Severec | 0 | 2
Cardiovascular
Vital Sign Changes During Administration
Bradycardia | <1 | <1
Hypotension | 5 | 5
Severe Cardiovascular Eventsc | 3 | 4
Abnormal ECG
All Patients | 60 | 52
Patients with Normal Baseline | 35 | 30
Respiratory
Cough | 7 | 6
Dyspnea | 12 | 9
Sensory Neuropathy
Any Symptoms | 71 | 56
Severe Symptomsc | 10 | 2
Myalgia / Arthralgia
Any Symptoms | 44 | 49
Severe Symptomsc | 8 | 4
Asthenia
Any Symptoms | 47 | 39
Severe Symptomsc | 8 | 3
Fluid Retention/Edema
Any Symptoms | 10 | 8
Severe Symptomsc | 0 | <1
Gastrointestinal
Nausea
Any Symptoms | 30 | 22
Severe Symptomsc | 3 | <1
Vomiting
Any Symptoms | 18 | 10
Severe Symptomsc | 4 | 1
Diarrhea
Any Symptoms | 27 | 15
Severe Symptomsc | <1 | 1
Mucositis
Any Symptoms | 7 | 6
Severe Symptomsc | <1 | 0
Alopecia | 90 | 94
Hepatic (Patients with Normal Baseline)
Bilirubin Elevations | 7 | 7
Alkaline Phosphatase Elevations | 36 | 31
AST (SGOT) Elevations | 39 | 32
Injection Site Reaction | <1 | 1
a Paclitaxel injection patients received premedication.
b Includes treatment-related events related to hypersensitivity (e.g., flushing, dyspnea, chest pain, hypotension) that began on a day of dosing.
c Severe events are defined as at least Grade 3 toxicity.

Other Adverse Reactions

Hematologic Disorders

Neutropenia was dose dependent and reversible. Among patients with metastatic breast cancer in the randomized trial, neutrophil counts declined below 500 cells/mm^3 (Grade 4) in 9% of the patients treated with a dose of 260 mg/m^2 compared to 22% in patients receiving paclitaxel injection at a dose of 175 mg/m^2. Pancytopenia has been observed in clinical trials.

Infections

Infectious episodes were reported in 24% of the patients treated with protein bound paclitaxel. Oral candidiasis, respiratory tract infections and pneumonia were the most frequently reported infectious complications.

Hypersensitivity Reactions (HSRs)

Grade 1 or 2 HSRs occurred on the day of protein bound paclitaxel administration and consisted of dyspnea (1%) and flushing, hypotension, chest pain, and arrhythmia (all <1%). The use of Paclitaxel Protein-Bound Particles for Injectable Suspension (Albumin-Bound) in patients previously exhibiting hypersensitivity to paclitaxel injection or human albumin has not been studied.

Cardiovascular

Hypotension, during the 30-minute infusion, occurred in 5% of patients. Bradycardia, during the 30-minute infusion, occurred in <1% of patients. These vital sign changes most often caused no symptoms and required neither specific therapy nor treatment discontinuation.

Severe cardiovascular events possibly related to single-agent protein bound paclitaxel occurred in approximately 3% of patients. These events included cardiac ischemia/infarction, chest pain, cardiac arrest, supraventricular tachycardia, edema, thrombosis, pulmonary thromboembolism, pulmonary emboli, and hypertension. Cases of cerebrovascular attacks (strokes) and transient ischemic attacks have been reported.

Electrocardiogram (ECG) abnormalities were common among patients at baseline. ECG abnormalities on study did not usually result in symptoms, were not dose-limiting, and required no intervention. ECG abnormalities were noted in 60% of patients. Among patients with a normal ECG prior to study entry, 35% of all patients developed an abnormal tracing while on study. The most frequently reported ECG modifications were non-specific repolarization abnormalities, sinus bradycardia, and sinus tachycardia.

Respiratory

Dyspnea (12%), cough (7%), and pneumothorax (<1%) were reported after treatment with protein bound paclitaxel.

Neurologic

The frequency and severity of sensory neuropathy increased with cumulative dose. Sensory neuropathy was the cause of protein bound paclitaxel discontinuation in 7/229 (3%) patients. Twenty-four patients (10%) treated with protein bound paclitaxel developed Grade 3 peripheral neuropathy; of these patients, 14 had documented improvement after a median of 22 days; 10 patients resumed treatment at a reduced dose of protein bound paclitaxel and 2 discontinued due to peripheral neuropathy. Of the 10 patients without documented improvement, 4 discontinued the study due to peripheral neuropathy.

No Grade 4 sensory neuropathies were reported. Only one incident of motor neuropathy (Grade 2) was observed in either arm of the controlled trial.

Vision Disorders

Ocular/visual disturbances occurred in 13% of all patients (n=366) treated with protein bound paclitaxel and 1% were severe. The severe cases (keratitis and blurred vision) were reported in patients who received higher doses than those recommended (300 or 375 mg/m^2). These effects generally have been reversible.

Arthralgia/Myalgia

The symptoms were usually transient, occurred two or three days after protein bound paclitaxel administration, and resolved within a few days.

Hepatic

Grade 3 or 4 elevations in GGT were reported for 14% of patients treated with protein bound paclitaxel and 10% of patients treated with paclitaxel injection in the randomized trial.

Renal

Overall 11% of patients experienced creatinine elevation, 1% severe. No discontinuations, dose reductions, or dose delays were caused by renal toxicities.

Other Clinical Events

Nail changes (changes in pigmentation or discoloration of nail bed) have been reported. Edema occurred in 10% of patients; no patients had severe edema. Dehydration and pyrexia were also reported.

Non-Small Cell Lung Cancer

Adverse reactions were assessed in 514 protein bound paclitaxel/carboplatin-treated patients and 524 paclitaxel injection/carboplatin-treated patients receiving first-line systemic treatment for locally advanced (stage IIIB) or metastatic (IV) non-small cell lung cancer (NSCLC) in a multicenter, randomized, open-label trial. Protein bound paclitaxel was administered as an intravenous infusion over 30 minutes at a dose of 100 mg/m^2 on Days 1, 8, and 15 of each 21-day cycle. Paclitaxel injection was administered as an intravenous infusion over 3 hours at a dose of 200 mg/m^2, following premedication. In both treatment arms carboplatin at a dose of AUC = 6 mg•min/mL was administered intravenously on Day 1 of each 21-day cycle after completion of protein bound paclitaxel/paclitaxel infusion.

The differences in paclitaxel dose and schedule between the two arms limit direct comparison of dose- and schedule-dependent adverse reactions. Among patients evaluable for adverse reactions, the median age was 60 years, 75% were men, 81% were White, 49% had adenocarcinoma, 43% had squamous cell lung cancer, 76% were ECOG PS 1. Patients in both treatment arms received a median of 6 cycles of treatment.

The following common (≥ 10% incidence) adverse reactions were observed at a similar incidence in protein bound paclitaxel plus carboplatin- treated and paclitaxel injection plus carboplatin-treated patients: alopecia 56%, nausea 27%, fatigue 25%, decreased appetite 17%, asthenia 16%, constipation 16%, diarrhea 15%, vomiting 12%, dyspnea 12%, and rash 10% (incidence rates are for the protein bound paclitaxel plus carboplatin treatment group).

Table 7 provides the frequency and severity of laboratory-detected abnormalities which occurred with a difference of ≥ 5% for all grades (1-4) or ≥ 2% for Grade 3-4 toxicity between protein bound paclitaxel plus carboplatin-treated patients or paclitaxel injection plus carboplatin-treated patients.

Table 7: Selected Hematologic Laboratory-Detected Abnormalities with a Difference of ≥ 5% for grades (1-4) or ≥ 2% for Grade 3-4 Toxicity Between Treatment Groups
 | Protein Bound Paclitaxel (100 mg/m^2 weekly) plus carboplatin |  | Paclitaxel Injection (200 mg/m^2 every 3 weeks) plus carboplatin
 | Grades 1-4 (%) | Grade 3-4 (%) | Grades 1-4 (%) | Grade 3-4 (%)
Anemia^1,2 | 98 | 28 | 91 | 7
Neutropenia^1,3 | 85 | 47 | 83 | 58
Thrombocytopenia^1,3 | 68 | 18 | 55 | 9
^1 508 patients assessed in protein bound paclitaxel/carboplatin-treated group.
^2 514 patients assessed in paclitaxel injection/carboplatin-treated group.
^3 513 patients assessed in paclitaxel injection/carboplatin-treated group.

Table 8 provides the frequency and severity of adverse reactions, which occurred with a difference of ≥ 5% for all grades (1-4) or ≥ 2% for Grade 3-4 between either treatment group for the 514 protein bound paclitaxel plus carboplatin-treated patients compared with the 524 patients who received paclitaxel injection plus carboplatin.

Table 8: Selected Adverse Reactions with a Difference of ≥5% for All Grade Toxicity or ≥2% for Grade 3-4 Toxicity Between Treatment Groups
System Organ Class | Adverse Reaction | Protein Bound Paclitaxel (100 mg/m^2 weekly) + carboplatin (N=514) |  | Paclitaxel Injection (200 mg/m^2 every 3 weeks) + carboplatin (N=524)
System Organ Class | Adverse Reaction | Grade 1-4 Toxicity (%) | Grade 3-4 Toxicity (%) | Grades 1-4 Toxicity (%) | Grade 3-4 Toxicity (%)
Nervous system disorders | Peripheral neuropathya | 48 | 3 | 64 | 12
General disorders and administration site conditions | Edema peripheral | 10 | 0 | 4 | <1
Respiratory thoracic and mediastinal disorders | Epistaxis | 7 | 0 | 2 | 0
Musculoskeletal and connective | Arthralgia | 13 | <1 | 25 | 2
tissue disorders | Myalgia | 10 | <1 | 19 | 2
a Peripheral neuropathy is defined by the MedDRA Version 14.0 SMQ neuropathy (broad scope).

For the protein bound paclitaxel plus carboplatin treated group, 17/514 (3%) patients developed Grade 3 peripheral neuropathy and no patients developed Grade 4 peripheral neuropathy. Grade 3 neuropathy improved to Grade 1 or resolved in 10/17 patients (59%) following interruption or discontinuation of protein bound paclitaxel.

Adenocarcinoma of the Pancreas

Adverse reactions were assessed in 421 patients who received protein bound paclitaxel plus gemcitabine and 402 patients who received gemcitabine for the first-line systemic treatment of metastatic adenocarcinoma of the pancreas in a multicenter, multinational, randomized, controlled, open-label trial. Patients received a median treatment duration of 3.9 months in the protein bound paclitaxel/gemcitabine group and 2.8 months in the gemcitabine group. For the treated population, the median relative dose intensity for gemcitabine was 75% in the protein bound paclitaxel /gemcitabine group and 85% in the gemcitabine group. The median relative dose intensity of protein bound paclitaxel was 81%.

Table 9 provides the frequency and severity of laboratory-detected abnormalities which occurred at a higher incidence for Grades 1- 4 (≥ 5%) or for Grade 3-4 (≥ 2%) toxicity in protein bound paclitaxel plus gemcitabine-treated patients.

Table 9: Selected Hematologic Laboratory-Detected Abnormalities with a Higher Incidence (≥ 5% for Grades 1-4 or ≥ 2% for Grades 3-4 Events) in the Protein Bound Paclitaxel/Gemcitabine Arm
 | Protein Bound Paclitaxel (125 mg/m^2)/ Gemcitabined |  | Gemcitabine
 | Grades 1-4 (%) | Grade 3-4 (%) | Grades 1-4 (%) | Grade 3-4 (%)
Neutropeniaa,b | 73 | 38 | 58 | 27
Thrombocytopeniab,c | 74 | 13 | 70 | 9
a 405 patients assessed in protein bound paclitaxel/gemcitabine-treated group.
b 388 patients assessed in gemcitabine-treated group.
c 404 patients assessed in protein bound paclitaxel/gemcitabine-treated group.
d Neutrophil growth factors were administered to 26% of patients in the protein bound paclitaxel /gemcitabine group.

Table 10 provides the frequency and severity of adverse reactions which occurred with a difference of ≥ 5% for all grades or ≥ 2% for Grade 3 or higher in the protein bound paclitaxel plus gemcitabine-treated group compared to the gemcitabine group.

Table 10: Selected Adverse Reactions with a Higher Incidence (≥5% for All Grade Toxicity or ≥2% for Grade 3 or Higher Toxicity) in the Protein Bound Paclitaxel/Gemcitabine Arm
System Organ Class | Adverse Reaction | Protein Bound Paclitaxel (125 mg/m^2) and gemcitabine (N=421) |  | Gemcitabine (N=402)
System Organ Class | Adverse Reaction | All Grades | Grade 3 or Higher | All Grades | Grade 3 or Higher
General disorders and administration site conditions | Fatigue | 248 (59%) | 77 (18%) | 183 (46%) | 37 (9%)
General disorders and administration site conditions | Peripheral edema | 194 (46%) | 13 (3%) | 122 (30%) | 12 (3%)
General disorders and administration site conditions | Pyrexia | 171 (41%) | 12 (3%) | 114 (28%) | 4 (1%)
General disorders and administration site conditions | Asthenia | 79 (19%) | 29 (7%) | 54 (13%) | 17 (4%)
General disorders and administration site conditions | Mucositis | 42 (10%) | 6 (1%) | 16 (4%) | 1 (<1%)
Gastrointestinal disorders | Nausea | 228 (54%) | 27 (6%) | 192 (48%) | 14 (3%)
Gastrointestinal disorders | Diarrhea | 184 (44%) | 26 (6%) | 95 (24%) | 6 (1%)
Gastrointestinal disorders | Vomiting | 151 (36%) | 25 (6%) | 113 (28%) | 15 (4%)
Skin and subcutaneous tissue disorders | Alopecia | 212 (50%) | 6 (1%) | 21 (5%) | 0
Skin and subcutaneous tissue disorders | Rash | 128 (30%) | 8 (2%) | 45 (11%) | 2 (<1%)
Nervous system disorders | Peripheral neuropathya | 227 (54%) | 70 (17%) | 51 (13%) | 3 (1%)
Nervous system disorders | Dysgeusia | 68 (16%) | 0 | 33 (8%) | 0
Nervous system disorders | Headache | 60 (14%) | 1 (<1%) | 38 (9%) | 1 (<1%)
Metabolism and nutrition disorders | Decreased appetite | 152 (36%) | 23 (5%) | 104 (26%) | 8 (2%)
Metabolism and nutrition disorders | Dehydration | 87 (21%) | 31 (7%) | 45 (11%) | 10 (2%)
Metabolism and nutrition disorders | Hypokalemia | 52 (12%) | 18 (4%) | 28 (7%) | 6 (1%)
Respiratory, thoracic and mediastinal disorders | Cough | 72 (17%) | 0 | 30 (7%) | 0
Respiratory, thoracic and mediastinal disorders | Epistaxis | 64 (15%) | 1 (<1%) | 14 (3%) | 1 (<1%)
Infections and infestations | Urinary tract infections b | 47 (11%) | 10 (2%) | 20 (5%) | 1 (<1%)
Musculoskeletal and connective tissue disorders | Pain in extremity | 48 (11%) | 3 (1%) | 24 (6%) | 3 (1%)
Musculoskeletal and connective tissue disorders | Arthralgia | 47 (11%) | 3 (1%) | 13 (3%) | 1 (<1%)
Musculoskeletal and connective tissue disorders | Myalgia | 44 (10%) | 4 (1%) | 15 (4%) | 0
Psychiatric disorders | Depression | 51 (12%) | 1 (<1%) | 24 (6%) | 0
a Peripheral neuropathy is defined by the MedDRA Version 15.0 Standard MedDRA Query neuropathy (broad scope).
b Urinary tract infections includes the preferred terms of: urinary tract infection, cystitis, urosepsis, urinary tract infection bacterial, and urinary tract infection enterococcal.

Additional clinically relevant adverse reactions that were reported in < 10% of the patients with adenocarcinoma of the pancreas who received protein bound paclitaxel/gemcitabine included:

Infections & infestations: oral candidiasis, pneumonia
Vascular disorders: hypertension
Cardiac disorders: tachycardia, congestive cardiac failure
Eye disorders: cystoid macular edema

Peripheral Neuropathy

Grade 3 peripheral neuropathy occurred in 17% of patients who received protein bound paclitaxel/gemcitabine compared to 1% of patients who received gemcitabine only; no patients developed grade 4 peripheral neuropathy. The median time to first occurrence of Grade 3 peripheral neuropathy in the protein bound paclitaxel arm was 140 days. Upon suspension of protein bound paclitaxel dosing, the median time to improvement from Grade 3 peripheral neuropathy to ≤ Grade 1 was 29 days. Of protein bound paclitaxel -treated patients with Grade 3 peripheral neuropathy, 44% resumed protein bound paclitaxel at a reduced dose.

Sepsis

Sepsis occurred in 5% of patients who received protein bound paclitaxel/gemcitabine compared to 2% of patients who received gemcitabine alone. Sepsis occurred both in patients with and without neutropenia. Risk factors for sepsis included biliary obstruction or presence of biliary stent.

Pneumonitis

Pneumonitis occurred in 4% of patients who received protein bound paclitaxel/gemcitabine compared to 1% of patients who received gemcitabine alone. Two of 17 patients in the protein bound paclitaxel arm with pneumonitis died.

6.2 Postmarketing Experience

The following adverse reactions have been identified during post-approval use of protein bound paclitaxel or with paclitaxel injection and may be expected to occur with protein bound paclitaxel. Because these reactions are reported voluntarily from a population of uncertain size, it is not always possible to reliably estimate their frequency or establish a causal relationship to drug exposure.

Hypersensitivity Reactions

Severe and sometimes fatal hypersensitivity reactions. Cross-hypersensitivity between protein bound and other taxanes has been reported.

Cardiovascular

Congestive heart failure, left ventricular dysfunction, and atrioventricular block. Most patients were previously exposed to cardiotoxic drugs, such as anthracyclines, or had underlying cardiac history.

Respiratory

Pneumonitis, interstitial pneumonia, and pulmonary embolism . Radiation pneumonitis in patients receiving concurrent radiotherapy. Lung fibrosis has been reported with paclitaxel injection.

Neurologic

Cranial nerve palsies and vocal cord paresis, as well as autonomic neuropathy resulting in paralytic ileus.

Vision Disorders

Reduced visual acuity due to cystoid macular edema (CME). After cessation of treatment, CME may improve, and visual acuity may return to baseline. Abnormal visual evoked potentials in patients treated with paclitaxel injection suggest persistent optic nerve damage.

Hepatic

Hepatic necrosis and hepatic encephalopathy leading to death in patients treated with paclitaxel injection.

Gastrointestinal (GI)

Intestinal obstruction, intestinal perforation, pancreatitis, and ischemic colitis. In patients treated with paclitaxel injection, neutropenic enterocolitis (typhlitis) despite the coadministration of G-CSF, alone and in combination with other chemotherapeutic agents.

Injection Site Reaction

Extravasation. Closely monitor the protein bound paclitaxel infusion site for possible infiltration during drug administration [see Dosage and Administration 2.1)].

Severe events such as phlebitis, cellulitis, induration, necrosis, and fibrosis have been reported with paclitaxel injection. In some cases, the onset of the injection site reaction occurred during a prolonged infusion or was delayed up to ten days. Recurrence of skin reactions at a site of previous extravasation following administration of paclitaxel injection at a different site has been reported.

Metabolic and Nutritional Disorders

Tumor lysis syndrome.

Other Clinical Events

Skin reactions including generalized or maculopapular rash, erythema, and pruritus.

Photosensitivity reactions, radiation recall phenomenon, scleroderma, and in some patients previously exposed to capecitabine, reports of palmar-plantar erythrodysesthesia. Stevens-Johnson syndrome and toxic epidermal necrolysis have been reported.

Conjunctivitis, cellulitis, and increased lacrimation have been reported with paclitaxel injection.

Accidental Exposure

Upon inhalation of paclitaxel, dyspnea, chest pain, burning eyes, sore throat, and nausea have been reported.

Following topical exposure, tingling, burning, and redness have been reported.

7 DRUG INTERACTIONS

The metabolism of paclitaxel is catalyzed by CYP2C8 and CYP3A4. Caution should be exercised when administering Paclitaxel Protein-Bound Particles for Injectable Suspension (Albumin-Bound) concomitantly with medicines known to inhibit or induce either CYP2C8 or CYP3A4.

8 USE IN SPECIFIC POPULATIONS

8.1 Pregnancy

Risk Summary

Based on its mechanism of action and findings in animals, Paclitaxel Protein-Bound Particles for Injectable Suspension (Albumin-Bound) can cause fetal harm when administered to a pregnant woman [see Clinical Pharmacology (12.1)]. There are no available human data on Paclitaxel Protein-Bound Particles for Injectable Suspension (Albumin-Bound) use in pregnant women to inform the drug-associated risk. In animal reproduction studies, administration of paclitaxel formulated as albumin-bound particles to pregnant rats during the period of organogenesis resulted in embryo-fetal toxicity at doses approximately 2% of the daily maximum recommended human dose on a mg/m^2 basis (see Data). Advise females of reproductive potential of the potential risk to a fetus.

The background rate of major birth defects and miscarriage is unknown for the indicated population. In the U.S. general population, the estimated background risk of major birth defects and miscarriage in clinically recognized pregnancies is 2% to 4% and 15% to 20%, respectively.

Data

Animal Data

In embryo-fetal development studies, intravenous administration of paclitaxel formulated as albumin-bound particles to rats during pregnancy, on gestation days 7 to 17 at doses of 6 mg/m^2 (approximately 2% of the daily maximum recommended human dose on a mg/m^2 basis) caused embryo-fetal toxicities, as indicated by intrauterine mortality, increased resorptions (up to 5-fold), reduced numbers of litters and live fetuses, reduction in fetal body weight, and increase in fetal anomalies. Fetal anomalies included soft tissue and skeletal malformations, such as eye bulge, folded retina, microphthalmia, and dilation of brain ventricles.

8.2 Lactation

Risk Summary

There are no data on the presence of paclitaxel in human milk, or its effect on the breastfed child or on milk production. In animal studies, paclitaxel and/or its metabolites were excreted into the milk of lactating rats (see Data). Because of the potential for serious adverse reactions in a breastfed child from Paclitaxel Protein-Bound Particles for Injectable Suspension (Albumin-Bound), advise lactating women not to breastfeed during treatment with Paclitaxel Protein-Bound Particles for Injectable Suspension (Albumin-Bound) and for two weeks after the last dose.

Data

Animal Data

Following intravenous administration of radiolabeled paclitaxel to rats on days 9 to 10 postpartum, concentrations of radioactivity in milk were higher than in plasma and declined in parallel with the plasma concentrations.

8.3 Females and Males of Reproductive Potential

Based on animal studies and mechanism of action, Paclitaxel Protein-Bound Particles for Injectable Suspension (Albumin-Bound) can cause fetal harm when administered to a pregnant woman [see Use in Specific Populations (8.1)].

Pregnancy Testing

Verify the pregnancy status of females of reproductive potential prior to starting treatment with Paclitaxel Protein-Bound Particles for Injectable Suspension (Albumin-Bound).

Contraception

Females

Advise females of reproductive potential to use effective contraception and avoid becoming pregnant during treatment with Paclitaxel Protein-Bound Particles for Injectable Suspension (Albumin-Bound) and for at least six months after the last dose.

Males

Based on findings in genetic toxicity and animal reproduction studies, advise males with female partners of reproductive potential to use effective contraception and avoid fathering a child during treatment with Paclitaxel Protein-Bound Particles for Injectable Suspension (Albumin-Bound) and for at least three months after the last dose [see Use in Specific Populations (8.1) and Nonclinical Toxicology (13.1)].

Infertility

Females and Males

Based on findings in animals, Paclitaxel Protein-Bound Particles for Injectable Suspension (Albumin-Bound) may impair fertility in females and males of reproductive potential [see Nonclinical Toxicology (13.1)].

8.4 Pediatric Use

Safety and effectiveness in pediatric patients have not been established. Pharmacokinetics, safety, and antitumor activity of protein bound paclitaxel were assessed in an open-label, dose escalation, dose expansion study (NCT01962103) in 96 pediatric patients aged 1.4 to < 17 years with recurrent or refractory pediatric solid tumors. The maximum tolerated dose (MTD) normalized for body surface area (BSA) was lower in pediatric patients compared to adults. No new safety signals were observed in pediatric patients across these studies.

Paclitaxel protein-bound exposures normalized by dose were higher in 96 pediatric patients (aged 1.4 to < 17 years) as compared to those in adults.

8.5 Geriatric Use

Of the 229 patients in the randomized study who received protein bound paclitaxel for the treatment of metastatic breast cancer, 13% were at least 65 years of age and < 2% were 75 years or older. This study of protein bound paclitaxel did not include a sufficient number of patients with metastatic breast cancer who were 65 years and older to determine whether they respond differently from younger patients.

A subsequent pooled analysis was conducted in 981 patients receiving protein bound paclitaxel monotherapy for metastatic breast cancer, of which 15% were 65 years of age or older and 2% were 75 years of age or older. A higher incidence of epistaxis, diarrhea, dehydration, fatigue, and peripheral edema was found in patients 65 years of age or older.

Of the 514 patients in the randomized study who received protein bound paclitaxel and carboplatin for the first-line treatment of non-small cell lung cancer, 31% were 65 years or older and 3.5% were 75 years or older. Myelosuppression, peripheral neuropathy, and arthralgia were more frequent in patients 65 years or older compared to patients younger than 65 years old. No overall difference in effectiveness, as measured by response rates, was observed between patients 65 years or older compared to patients younger than 65 years old.

Of the 431 patients in the randomized study who received protein bound paclitaxel and gemcitabine for the first-line treatment of pancreatic adenocarcinoma, 41% were 65 years or older and 10% were 75 years or older. No overall differences in effectiveness were observed between patients who were 65 years of age or older and younger patients. Diarrhea, decreased appetite, dehydration, and epistaxis were more frequent in patients 65 years or older compared with patients younger than 65 years old. Clinical studies of protein bound paclitaxel did not include sufficient number of patients with pancreatic cancer who were 75 years and older to determine whether they respond differently from younger patients.

8.6 Renal Impairment

No adjustment of the starting Paclitaxel Protein-Bound Particles for Injectable Suspension (Albumin-Bound) dose is required for patients with mild to moderate renal impairment (estimated creatinine clearance 30 to <90 mL/min) [see Clinical Pharmacology (12.3)]. There are insufficient data to permit dosage recommendations in patients with severe renal impairment or end stage renal disease (estimated creatinine clearance <30 mL/min).

8.7 Hepatic Impairment

No adjustment of the starting Paclitaxel Protein-Bound Particles for Injectable Suspension (Albumin-Bound) dose is required for patients with mild hepatic impairment (total bilirubin > ULN and ≤ 1.5 x ULN and aspartate aminotransferase [AST] ≤ 10 x ULN). Reduce Paclitaxel Protein-Bound Particles for Injectable Suspension (Albumin-Bound) starting dose in patients with moderate to severe hepatic impairment [see Dosage and Administration (2.5) and Clinical Pharmacology (12.3)]. Paclitaxel Protein-Bound Particles for Injectable Suspension (Albumin-Bound) is not recommended for use in patients with total bilirubin > 5 x ULN or AST > 10 x ULN [see Dosage and Administration (2.5), Warnings and Precautions (5.6), and Clinical Pharmacology (12.3)]. Paclitaxel Protein-Bound Particles for Injectable Suspension (Albumin-Bound) is not recommended for use in patients with metastatic adenocarcinoma of the pancreas who have moderate to severe hepatic impairment [see Dosage and Administration (2.5)].

10 OVERDOSAGE

There is no known antidote for Paclitaxel Protein-Bound Particles for Injectable Suspension (Albumin-Bound) overdosage. The primary anticipated complications of overdosage would consist of bone marrow suppression, sensory neurotoxicity, and mucositis.

11 DESCRIPTION

Paclitaxel Protein-Bound Particles for Injectable Suspension (Albumin-Bound) is paclitaxel formulated as albumin‑bound nanoparticles with a mean particle size of approximately 130 nanometers. Paclitaxel exists in the particles in a non-crystalline, amorphous state. Paclitaxel is a microtubule inhibitor. The chemical name for paclitaxel is 5β,20 Epoxy-1,2α,4,7β,10β,13α-hexahydroxytax-11-en-9-one 4,10-diacetate 2-benzoate 13-ester with (2R,3S)-N-benzoyl-3-phenylisoserine. The empirical formula is C47H51NO14 and the molecular weight is 853.91. Paclitaxel has the following structural formula:

Paclitaxel is a white to off-white crystalline powder. It is highly lipophilic, insoluble in water, and melts at approximately 216°C to 217°C.

Paclitaxel Protein-Bound Particles for Injectable Suspension (Albumin-Bound) is supplied as a white to yellow, sterile, lyophilized powder for reconstitution with 20 mL of 0.9% Sodium Chloride Injection, USP prior to intravenous infusion. Each single‑dose vial contains 100 mg of paclitaxel (bound to human albumin) and approximately 900 mg of human albumin (containing sodium caprylate and sodium acetyltryptophanate), and sodium hydroxide and hydrochloric acid for pH adjustment. Each milliliter (mL) of reconstituted suspension contains 5 mg paclitaxel formulated as albumin‑bound particles. Paclitaxel Protein-Bound Particles for Injectable Suspension (Albumin-Bound) is free of solvents.

12 CLINICAL PHARMACOLOGY

12.1 Mechanism of Action

Paclitaxel Protein-Bound Particles for Injectable Suspension (Albumin-Bound) is a microtubule inhibitor that promotes the assembly of microtubules from tubulin dimers and stabilizes microtubules by preventing depolymerization. This stability results in the inhibition of the normal dynamic reorganization of the microtubule network that is essential for vital interphase and mitotic cellular functions. Paclitaxel induces abnormal arrays or “bundles” of microtubules throughout the cell cycle and multiple asters of microtubules during mitosis.

12.3 Pharmacokinetics

The pharmacokinetics of total paclitaxel following 30 and 180-minute infusions of protein bound paclitaxel at dose levels of 80 to 375 mg/m^2 (0.31 to 1.15 times the maximum approved recommended dosage) were determined in clinical studies. Dose levels of mg/m^2 refer to mg of paclitaxel in protein bound paclitaxel. Following intravenous administration of protein bound paclitaxel to patients with solid tumors, paclitaxel plasma concentrations declined in a biphasic manner, the initial rapid decline representing distribution to the peripheral compartment and the slower second phase representing drug elimination.

Following protein bound paclitaxel infusion, paclitaxel exhibited linear drug exposure (AUC) across clinical doses ranging from 80 to 300 mg/m^2 (0.31 to 1.15 times the maximum approved recommended dosage). The pharmacokinetics of paclitaxel in protein bound paclitaxel were independent of the duration of intravenous administration.

The pharmacokinetic data of 260 mg/m^2 protein bound paclitaxel administered over a 30-minute infusion was compared to the pharmacokinetics of 175 mg/m^2 paclitaxel injection over a 3-hour infusion. Clearance was larger (43%) and the volume of distribution was higher (53%) for protein bound paclitaxel than for paclitaxel injection. There were no differences in terminal half-lives.

Distribution

Following protein bound paclitaxel administration to patients with solid tumors, paclitaxel is evenly distributed into blood cells and plasma and is highly bound to plasma proteins (94%). The total volume of distribution is approximately 1741 L; the large volume of distribution indicates extensive extravascular distribution and/or tissue binding of paclitaxel.

In a within-patient comparison study, the fraction of unbound paclitaxel in plasma was significantly higher with protein bound paclitaxel (6.2%) than with solvent-based paclitaxel (2.3%). This contributes to significantly higher exposure to unbound paclitaxel with protein bound paclitaxel compared with solvent-based paclitaxel, when the total exposure is comparable. In vitro studies of binding to human serum proteins, using paclitaxel concentrations ranging from 0.1 to 50 μg/mL, indicated that the presence of cimetidine, ranitidine, dexamethasone, or diphenhydramine did not affect protein binding of paclitaxel.

Elimination

At the clinical dose range of 80 to 300 mg/m^2 (0.31 to 1.15 times the maximum approved recommended dosage), the mean total clearance of paclitaxel ranges from 13 to 30 L/h/m^2 and the mean terminal half-life ranges from 13 to 27 hours.

Metabolism

In vitro studies with human liver microsomes and tissue slices showed that paclitaxel in protein bound paclitaxel was metabolized primarily to 6α-hydroxypaclitaxel by CYP2C8; and to two minor metabolites, 3'-p-hydroxypaclitaxel and 6α, 3'-p-dihydroxypaclitaxel, by CYP3A4. In vitro, the metabolism of paclitaxel to 6α-hydroxypaclitaxel was inhibited by a number of agents (ketoconazole, verapamil, diazepam, quinidine, dexamethasone, cyclosporin, teniposide, etoposide, and vincristine), but the concentrations used exceeded those found in vivo following normal therapeutic doses. Testosterone, 17α-ethinyl estradiol, retinoic acid, and quercetin, a specific inhibitor of CYP2C8, also inhibited the formation of 6α-hydroxypaclitaxel in vitro. The pharmacokinetics of paclitaxel may also be altered in vivo as a result of interactions with compounds that are substrates, inducers, or inhibitors of CYP2C8 and/or CYP3A4 [see Drug Interactions (7)].

Excretion

After a 30-minute infusion of 260 mg/m^2 doses of protein bound paclitaxel, the mean values for cumulative urinary recovery of unchanged drug (4%) indicated extensive non-renal clearance. Less than 1% of the total administered dose was excreted in urine as the metabolites 6α-hydroxypaclitaxel and 3'-p-hydroxypaclitaxel. Fecal excretion was approximately 20% of the total dose administered.

Specific Populations

No clinically meaningful differences in the pharmacokinetics of paclitaxel in protein bound paclitaxel were observed based on body weight (40 to 143 kg), body surface area (1.3 to 2.4 m^2), sex, race (Asian vs. White), age (24 to 85 years), type of solid tumors, mild to moderate renal impairment (creatinine clearance 30 to <90 mL/min), and mild hepatic impairment (total bilirubin >1 to ≤1.5 x ULN and AST ≤10 x ULN).

Patients with moderate (total bilirubin >1.5 to 3 x ULN and AST ≤10 x ULN) or severe (total bilirubin >3 to 5 x ULN) hepatic impairment had a 22% to 26% decrease in the maximum elimination rate of paclitaxel and approximately 20% increase in mean paclitaxel AUC compared with patients with normal hepatic function (total bilirubin ≤ULN and AST ≤ULN) [see Dosage and Administration (2.5) and Use in Specific Populations (8.7)].

The effect of severe renal impairment or end stage renal disease (creatinine clearance < 30 mL/min) on the pharmacokinetics of paclitaxel in protein bound paclitaxel is unknown.

Drug Interaction Studies

Carboplatin: Administration of carboplatin immediately after the completion of the protein bound paclitaxel infusion to patients with NSCLC did not cause clinically meaningful changes in paclitaxel exposure. The observed mean AUCinf of free carboplatin was approximately 23% higher than the targeted value (6 min*mg/mL), but its mean half-life and clearance were consistent with those reported in the absence of paclitaxel.

13 NONCLINICAL TOXICOLOGY

13.1 Carcinogenesis, Mutagenesis, Impairment of Fertility

The carcinogenic potential of Paclitaxel Protein-Bound Particles for Injectable Suspension (Albumin-Bound) has not been studied.

Paclitaxel was clastogenic in vitro (chromosome aberrations in human lymphocytes) and in vivo (micronucleus test in mice). Paclitaxel was not mutagenic in the Ames test or the CHO/HGPRT gene mutation assay.

Administration of paclitaxel formulated as albumin-bound particles to male rats at 42 mg/m^2 on a weekly basis (approximately 16% of the daily maximum recommended human exposure on a body surface area basis) for 11 weeks prior to mating with untreated female rats resulted in significantly reduced fertility accompanied by decreased pregnancy rates and increased loss of embryos in mated females. A dose of 42 mg/m^2 also reduced male reproductive organ weights, mating performance, and sperm production. Testicular atrophy/degeneration was observed in single-dose toxicology studies in animals administered paclitaxel formulated as albumin-bound particles at doses lower than the recommended human dose; doses were 54 mg/m^2 in rodents and 175 mg/m^2 in dogs. Similar testicular degeneration was seen in monkeys administered three weekly doses of 108 mg/m^2 paclitaxel formulated as albumin bound particles.

Administration of paclitaxel prior to and during mating produced impairment of fertility in male and female rats. Paclitaxel caused reduced fertility and reproductive indices, and increased embryo-fetal toxicity.

14 CLINICAL STUDIES

14.1 Metastatic Breast Cancer

Data from 106 patients accrued in two single arm open label studies and from 460 patients enrolled in a randomized comparative study were available to support the use of protein bound paclitaxel in metastatic breast cancer.

Single Arm Open Label Studies

In one study, protein bound paclitaxel was administered as a 30-minute infusion at a dose of 175 mg/m^2 to 43 patients with metastatic breast cancer. The second trial utilized a dose of 300 mg/m^2 as a 30-minute infusion in 63 patients with metastatic breast cancer. Cycles were administered at 3-week intervals. Objective responses were observed in both studies.

Randomized Comparative Study

This multicenter trial was conducted in 460 patients with metastatic breast cancer. Patients were randomized to receive protein bound paclitaxel at a dose of 260 mg/m^2 given as a 30-minute infusion, or paclitaxel injection at 175 mg/m^2 given as a 3-hour infusion. Sixty-four percent of patients had impaired performance status (ECOG 1 or 2) at study entry; 79% had visceral metastases; and 76% had > 3 sites of metastases. Fourteen percent of the patients had not received prior chemotherapy; 27% had received chemotherapy in the adjuvant setting, 40% in the metastatic setting and 19% in both metastatic and adjuvant settings. Fifty-nine percent received study drug as second or greater than second-line therapy. Seventy-seven percent of the patients had been previously exposed to anthracyclines.

In this trial, patients in the protein bound paclitaxel treatment arm had a statistically significantly higher reconciled target lesion response rate (the trial primary endpoint) of 21.5% (95% CI: 16.2% to 26.7%), compared to 11.1% (95% CI: 6.9% to 15.1%) for patients in the paclitaxel injection treatment arm. See Table 11. There was no statistically significant difference in overall survival between the two study arms.

Table 11: Efficacy Results from Randomized Metastatic Breast Cancer Trial
 |  | Protein Bound Paclitaxel 260 mg/m^2 | Paclitaxel Injection 175 mg/m^2
Reconciled Target Lesion Response Rate (primary endpoint) a
All randomized patients | Response Rate [95% CI] | 50/233 (21.5%) [16.19% – 26.73%] | 25/227 (11.1%) [6.94% – 15.09%]
All randomized patients | p-valueb | 0.003
Patients who had failed combination chemotherapy or relapsed within 6 months of adjuvant chemotherapyc | Response Rate [95% CI] | 20/129 (15.5%) [9.26% – 21.75%] | 12/143 (8.4%) [3.85% – 12.94%]
a Reconciled Target Lesion Response Rate (TLRR) was the prospectively defined protocol specific endpoint, based on independent radiologic assessment of tumor responses reconciled with investigator responses (which also included clinical information) for the first 6 cycles of therapy. The reconciled TLRR was lower than the investigator Reported Response Rates, which are based on all cycles of therapy.
b From Cochran-Mantel-Haenszel test stratified by 1st line vs. > 1st line therapy.
c Prior therapy included an anthracycline unless clinically contraindicated.

14.2 Non-Small Cell Lung Cancer

A multicenter, randomized, open-label study was conducted in 1052 chemotherapy naive patients with Stage IIIb/IV non-small cell lung cancer to compare protein bound paclitaxel in combination with carboplatin to paclitaxel injection in combination with carboplatin as first- line treatment in patients with advanced non-small cell lung cancer. Protein bound paclitaxel was administered as an intravenous infusion over 30 minutes at a dose of 100 mg/m^2 on Days 1, 8, and 15 of each 21-day cycle. Paclitaxel injection was administered as an intravenous infusion over 3 hours at a dose of 200 mg/m^2, following premedication. In both treatment arms carboplatin at a dose of AUC = 6 mg•min/mL was administered intravenously on Day 1 of each 21-day cycle after completion of protein bound paclitaxel/paclitaxel infusion. Treatment was administered until disease progression or development of an unacceptable toxicity. The major efficacy outcome measure was overall response rate as determined by a central independent review committee using RECIST guidelines (Version 1.0).

In the intent-to-treat (all-randomized) population, the median age was 60 years, 75% were men, 81% were White, 49% had adenocarcinoma, 43% had squamous cell lung cancer, 76% were ECOG PS 1, and 73% were current or former smokers. Patients received a median of 6 cycles of treatment in both study arms.

Patients in the protein bound paclitaxel/carboplatin arm had a statistically significantly higher overall response rate compared to patients in the paclitaxel injection/carboplatin arm [(33% versus 25%) see Table 12]. There was no statistically significant difference in overall survival between the two study arms.

Table 12: Efficacy Results from Randomized Non-Small Cell Lung Cancer Trial (Intent-to-Treat Population)
 | Protein Bound Paclitaxel (100 mg/m^2 weekly) + carboplatin (N=521) | Paclitaxel Injection (200 mg/m^2 every 3 weeks) + carboplatin (N=531)
Overall Response Rate (ORR)
Confirmed complete or partial overall response, n (%) | 170 (33%) | 132 (25%)
95% CI | 28.6, 36.7 | 21.2, 28.5
P-value (Chi-Square test) | 0.005
Median DoR in months (95% CI) | 6.9 (5.6, 8.0) | 6.0 (5.6, 7.1)
Overall Response Rate by Histology
Carcinoma/Adenocarcinoma | 66/254 (26%) | 71/264 (27%)
Squamous Cell Carcinoma | 94/229 (41%) | 54/221 (24%)
Large Cell Carcinoma | 3/9 (33%) | 2/13 (15%)
Other | 7/29 (24%) | 5/33 (15%)
CI = confidence interval; DoR= Duration of response.

14.3 Adenocarcinoma of the Pancreas

A multicenter, multinational, randomized, open-label study was conducted in 861 patients comparing protein bound paclitaxel plus gemcitabine versus gemcitabine monotherapy as first-line treatment of metastatic adenocarcinoma of the pancreas. Key eligibility criteria were Karnofsky Performance Status (KPS) ≥70, normal bilirubin level, transaminase levels ≤ 2.5 times the upper limit of normal (ULN) or ≤ 5 times the ULN for patients with liver metastasis, no prior cytotoxic chemotherapy in the adjuvant setting or for metastatic disease, no ongoing active infection requiring systemic therapy, and no history of interstitial lung disease. Patients with rapid decline in KPS (≥10%) or serum albumin (≥20%) during the 14 day screening period prior to study randomization were ineligible.

A total of 861 patients were randomized (1:1) to the protein bound paclitaxel/gemcitabine arm (N=431) or to the gemcitabine arm (N=430).

Randomization was stratified by geographic region (Australia, Western Europe, Eastern Europe, or North America), KPS (70 to 80 versus 90 to 100), and presence of liver metastasis (yes versus no). Patients randomized to protein bound paclitaxel/gemcitabine received protein bound paclitaxel 125 mg/m^2 as an intravenous infusion over 30-40 minutes followed by gemcitabine 1000 mg/m^2 as an intravenous infusion over 30-40 minutes on Days 1, 8, and 15 of each 28-day cycle. Patients randomized to gemcitabine received 1000 mg/m^2 as an intravenous infusion over 30-40 minutes weekly for 7 weeks followed by a 1-week rest period in Cycle 1 then as 1000 mg/m^2 on Days 1, 8 and 15 of each subsequent 28-day cycle. Patients in both arms received treatment until disease progression or unacceptable toxicity. The major efficacy outcome measure was overall survival (OS). Additional outcome measures were progression-free survival (PFS) and overall response rate (ORR), both assessed by independent, central, blinded radiological review using RECIST (version 1.0).

In the intent-to-treat (all randomized) population, the median age was 63 years (range 27-88 years) with 42% ≥ 65 years of age; 58% were men; 93% were White and KPS was 90-100 in 60%. Disease characteristics included 46% of patients with 3 or more metastatic sites; 84% of patients had liver metastasis; and the location of the primary pancreatic lesion was in the head of pancreas (43%), body (31%), or tail (25%).

Results for overall survival, progression-free survival, and overall response rate are shown in Table 13.

Table 13: Efficacy Results from Randomized Study in Patients with Adenocarcinoma of the Pancreas (ITT Population)
 | Protein Bound Paclitaxel (125 mg/m^2) and gemcitabine (N = 431) | Gemcitabine (N = 430)
Overall Survival
Number of deaths, n (%) | 333 (77) | 359 (83)
Median Overall Survival (months) | 8.5 | 6.7
95% CI | 7.9, 9.5 | 6.0, 7.2
HR (95% CI) a | 0.72 (0.62, 0.83)
P-valueb | <0.0001
Progression-free Survivalc
Death or progression, n (%) | 277 (64) | 265 (62)
Median Progression-free Survival (months) | 5.5 | 3.7
95% CI | 4.5, 5.9 | 3.6, 4.0
HR (95% CI) a | 0.69 (0.58, 0.82)
P-valueb | <0.0001
Overall Response Ratec
Confirmed complete or partial overall response, n (%) | 99 (23) | 31 (7)
95% CI | 19.1, 27.2 | 5.0, 10.1
P-value d | <0.0001
CI = confidence interval, HR = hazard ratio of protein bound paclitaxel plus gemcitabine / gemcitabine, ITT = intent-to-treat population.
a Stratified Cox proportional hazard model.
b Stratified log-rank test stratified by geographic region (North America versus Others), Karnofsky performance score (70 to 80 versus 90 to 100), and presence of liver metastasis (yes versus no).
c Based on Independent Radiological Reviewer Assessment.
d Chi-square test.

In exploratory analyses conducted in clinically relevant subgroups with a sufficient number of subjects, the treatment effects on overall survival were similar to that observed in the overall study population.

Figure 1: Kaplan-Meier Curve of Overall Survival (Intent-to-Treat Population)

15 REFERENCES

1. OSHA Hazardous Drugs. OSHA http://www.osha.gov/SLTC/hazardousdrugs/index.html

16 HOW SUPPLIED/STORAGE AND HANDLING

Paclitaxel Protein-Bound Particles for Injectable Suspension (Albumin-Bound) is a white to yellow, sterile, lyophilized powder supplied as:

NDC: 0517-4300-01 100 mg of paclitaxel in a single-dose vial, individually packaged in a carton.

Store the vials in original cartons at 20°C to 25°C (68°F to 77°F) (see USP Controlled Room Temperature). Retain in the original package to protect from bright light. Paclitaxel Protein-Bound Particles for Injectable Suspension (Albumin-Bound) is a hazardous drug. Follow applicable special handling and disposal procedures.^1

17 PATIENT COUNSELING INFORMATION

Advise the patient to read the FDA-approved patient labeling (Patient Information).

Severe Myelosuppression

- Patients must be informed of the risk of low blood cell counts and severe and life-threatening infections and instructed to contact their healthcare provider immediately for fever or evidence of infection [see Warnings and Precautions (5.1), (5.3)].

Severe Neuropathy

- Patients must be informed that sensory neuropathy occurs frequently with Paclitaxel Protein-Bound Particles for Injectable Suspension (Albumin-Bound) and patients should advise their healthcare providers of numbness, tingling, pain or weakness involving the extremities [see Warnings and Precautions (5.2)].

Pneumonitis

- Instruct patients to contact their healthcare provider immediately for sudden onset of dry persistent cough, or shortness of breath [see Warnings and Precautions (5.4)].

Severe Hypersensitivity

- Instruct patients to contact their healthcare provider for signs of an allergic reaction, which could be severe and sometimes fatal [see Warnings and Precautions (5.5)].

Common Adverse Reactions

- Explain to patients that alopecia, fatigue/asthenia, and myalgia/arthralgia occur frequently with Paclitaxel Protein-Bound Particles for Injectable Suspension (Albumin-Bound).
- Instruct patients to contact their healthcare providers for persistent vomiting, diarrhea, or signs of dehydration [see Adverse Reactions (6)].

Embryo-Fetal Toxicity

- Paclitaxel Protein-Bound Particles for Injectable Suspension (Albumin-Bound) injection can cause fetal harm. Advise patients to avoid becoming pregnant while receiving this drug. Females of reproductive potential should use effective contraception during treatment with Paclitaxel Protein-Bound Particles for Injectable Suspension (Albumin-Bound) and for at least six months after the last dose of Paclitaxel Protein-Bound Particles for Injectable Suspension (Albumin-Bound) [see Warnings and Precautions (5.8) and Use in Specific Populations (8.1, 8.3)].
- Advise male patients with female partners of reproductive potential to use effective contraception and avoid fathering a child during treatment with Paclitaxel Protein-Bound Particles for Injectable Suspension (Albumin-Bound) and for at least three months after the last dose of Paclitaxel Protein-Bound Particles for Injectable Suspension (Albumin-Bound) [see Use in Specific Populations (8.3)].

Lactation

- Advise patients not to breastfeed while taking Paclitaxel Protein-Bound Particles for Injectable Suspension (Albumin-Bound) and for two weeks after receiving the last dose [see Use in Specific Populations (8.2)].

Infertility

- Advise males and females of reproductive potential that Paclitaxel Protein-Bound Particles for Injectable Suspension (Albumin-Bound) may impair fertility [see Use in Specific Populations (8.3)].

Patient Information
Paclitaxel Protein-Bound Particles for Injectable Suspension (Albumin-Bound)

What is Paclitaxel Protein-Bound Particles for Injectable Suspension (Albumin-Bound)?
Paclitaxel Protein-Bound Particles for Injectable Suspension (Albumin-Bound) is a prescription medicine used to treat:

- advanced breast cancer in people who have already received certain other medicines for their cancer.
- advanced non-small cell lung cancer (NSCLC), in combination with carboplatin in people who cannot be treated with surgery or radiation.
- advanced pancreatic cancer, when used in combination with gemcitabine as the first medicine for advanced pancreatic cancer.

It is not known if Paclitaxel Protein-Bound Particles for Injectable Suspension (Albumin-Bound) is safe or effective in children.

Do not receive Paclitaxel Protein-Bound Particles for Injectable Suspension (Albumin-Bound) if:

- your white blood cell count is below 1,500 cells/ mm^3.
- you have had a severe allergic reaction to Paclitaxel Protein-Bound Particles for Injectable Suspension (Albumin-Bound).

Before you receive Paclitaxel Protein-Bound Particles for Injectable Suspension (Albumin-Bound), tell your healthcare provider about all of your medical conditions, including if you:

- have liver or kidney problems.
- had a prior allergic reaction to a taxane.
- are pregnant or plan to become pregnant. Paclitaxel Protein-Bound Particles for Injectable Suspension (Albumin-Bound) can harm your unborn baby.
  Females who are able to become pregnant:
  - Your healthcare provider will check to see if you are pregnant before you start treatment with Paclitaxel Protein-Bound Particles for Injectable Suspension (Albumin-Bound).
  - You should not become pregnant during your treatment and for at least six months after the last dose of Paclitaxel Protein-Bound Particles for Injectable Suspension (Albumin-Bound).
  - You should use effective birth control (contraception) during your treatment and for at least six months after the last dose of Paclitaxel Protein-Bound Particles for Injectable Suspension (Albumin-Bound). Talk to your healthcare provider about birth control methods you can use during this time.
  Males with a female sexual partner who can become pregnant:
  - Paclitaxel Protein-Bound Particles for Injectable Suspension (Albumin-Bound) can harm the unborn baby of your partner.
  - You should not father a child during your treatment and for at least three months after the last dose of Paclitaxel Protein-Bound Particles for Injectable Suspension (Albumin-Bound).
  - You should use effective birth control (contraception) during your treatment and for at least three months after the last dose of Paclitaxel Protein-Bound Particles for Injectable Suspension (Albumin-Bound).
- are breastfeeding or plan to breastfeed. Do not breastfeed during your treatment and for two weeks after the last dose of Paclitaxel Protein-Bound Particles for Injectable Suspension (Albumin-Bound).

Tell your healthcare provider about all the medicines you take, including prescription and over-the-counter medicines, vitamins, and herbal supplements.
Know the medicines you take. Keep a list to show your healthcare provider and pharmacist when you get a new medicine.

How will I receive Paclitaxel Protein-Bound Particles for Injectable Suspension (Albumin-Bound)?

- Your healthcare provider will prescribe Paclitaxel Protein-Bound Particles for Injectable Suspension (Albumin-Bound) in an amount that is right for you.
- Your healthcare provider may give you certain medicines to help prevent allergic reactions if you have had an allergic reaction to Paclitaxel Protein-Bound Particles for Injectable Suspension (Albumin-Bound) in the past.
- Paclitaxel Protein-Bound Particles for Injectable Suspension (Albumin-Bound) will be given to you by intravenous (IV) infusion into your vein.
- Your healthcare provider should do blood tests regularly during treatment with Paclitaxel Protein-Bound Particles for Injectable Suspension (Albumin-Bound).
- Your healthcare provider may stop your treatment, delay your treatment, or change your dose of Paclitaxel Protein-Bound Particles for Injectable Suspension (Albumin-Bound) if you have certain side effects.

What are the possible side effects of Paclitaxel Protein-Bound Particles for Injectable Suspension (Albumin-Bound)? Paclitaxel Protein-Bound Particles for Injectable Suspension (Albumin-Bound) may cause serious side effects, including:

- severe decreased blood cell counts. Paclitaxel Protein-Bound Particles for Injectable Suspension (Albumin-Bound) can cause a severe decrease in neutrophils, a type of white blood cell which helps fight infections, and blood cells called platelets which help to clot blood. Your healthcare provider will check your blood cell count during your treatment with Paclitaxel Protein-Bound Particles for Injectable Suspension (Albumin-Bound).
- severe nerve problems (neuropathy). Tell your healthcare provider if you have numbness, tingling, pain, or weakness in your hands or feet.
- severe infection (sepsis). If you receive Paclitaxel Protein-Bound Particles for Injectable Suspension (Albumin-Bound) in combination with gemcitabine, infections can be severe and lead to death. Tell your healthcare provider right away if you have a fever (temperature greater than 100.4° F) or develop signs of infection.
- lung or breathing problems. If you receive Paclitaxel Protein-Bound Particles for Injectable Suspension (Albumin-Bound) in combination with gemcitabine, lung or breathing problems may be severe and can lead to death. Tell your healthcare provider right away if you suddenly get a dry cough that will not go away or shortness of breath.
- severe allergic reactions. Severe allergic reactions are medical emergencies that can happen in people who receive Paclitaxel Protein-Bound Particles for Injectable Suspension (Albumin-Bound) and can lead to death. You may have an increased risk of having an allergic reaction to Paclitaxel Protein-Bound Particles for Injectable Suspension (Albumin-Bound) if you are allergic to other taxane medicines. Your healthcare provider will monitor you closely for allergic reactions during your infusion of Paclitaxel Protein-Bound Particles for Injectable Suspension (Albumin-Bound). Tell your healthcare provider right away if you get any of these signs of a serious allergic reaction: trouble breathing, sudden swelling of your face, lips, tongue, throat, or trouble swallowing, hives (raised bumps), rash, or redness all over your body.

The most common side effects of Paclitaxel Protein-Bound Particles for Injectable Suspension (Albumin-Bound) in people with breast cancer include:

- hair loss
- numbness, tingling, pain, weakness in the hands or feet
- tiredness
- changes in your liver function tests
- nausea
- diarrhea
- infections

- decreased white blood cell count
- abnormal heartbeat
- joint and muscle pain
- low red blood cell count (anemia). Red blood cells carry oxygen to your body tissues. Tell your healthcare provider if you feel weak, tired or short of breath.

The most common side effects of Paclitaxel Protein-Bound Particles for Injectable Suspension (Albumin-Bound) in people with non-small cell lung cancer include:

- low red blood cell count (anemia)
- decreased platelet cell count
- numbness, tingling, pain, or weakness in the hands or feet
- tiredness

- decreased white blood cell count
- hair loss
- nausea

The most common side effects of Paclitaxel Protein-Bound Particles for Injectable Suspension (Albumin-Bound) in people with pancreatic cancer include:

- decreased white blood cell count
- numbness, tingling, pain, or weakness in the hands or feet
- hair loss
- diarrhea
- vomiting
- rash

- tiredness
- nausea
- swelling in the hands or feet
- fever
- decreased appetite
- signs of dehydration including, thirst, dry mouth, dark yellow urine, decreased urine, headache, or muscle cramps

Tell your healthcare provider if you have vomiting, diarrhea or signs of dehydration that does not go away.
Paclitaxel Protein-Bound Particles for Injectable Suspension (Albumin-Bound) may cause fertility problems in males and females, which may affect your ability to have a child. Talk to your healthcare provider if this is a concern for you. These are not all the possible side effects of Paclitaxel Protein-Bound Particles for Injectable Suspension (Albumin-Bound).
Call your doctor for medical advice about side effects. You may report side effects to FDA at 1-800-FDA-1088.

General information about the safe and effective use of Paclitaxel Protein-Bound Particles for Injectable Suspension (Albumin-Bound).
Medicines are sometimes prescribed for purposes other than those listed in a Patient Information leaflet. You can ask your healthcare provider or pharmacist for information about Paclitaxel Protein-Bound Particles for Injectable Suspension (Albumin-Bound) that is written for health professionals.

What are the ingredients in Paclitaxel Protein-Bound Particles for Injectable Suspension (Albumin-Bound)?
Active ingredient: paclitaxel (bound to human albumin).
Other ingredient: human albumin (containing sodium caprylate and sodium acetyltryptophanate), sodium hydroxide, and hydrochloric acid.
Manufactured for: American Regent, Inc.,
Shirley, NY 11967
For more information, call 1-888-532-7998.

This Patient Information has been approved by the U.S. Food and Drug Administration. Issued: 07/2022

Principal Display Panel - Vial Label

NDC 0517-4300-01

Paclitaxel
Protein-Bound Particles
for Injectable Suspension
(Albumin-Bound)

100 mg per vial

Single-Dose Vial

Discard any unused portion.

For Intravenous Use Only

Rx only

Do not substitute Paclitaxel Protein-Bound
Particles for other non-protein-bound
paclitaxel products.

Principal Display Panel - Printed Carton

NDC 0517-4300-01

Read all sides of carton.

Paclitaxel
Protein-Bound Particles
for Injectable Suspension
(Albumin-Bound)

100 mg per vial

Single-Dose Vial

Discard any unused portion.

For Intravenous Use Only

Rx only

Do not substitute Paclitaxel Protein-Bound
Particles for other non-protein-bound
paclitaxel products.